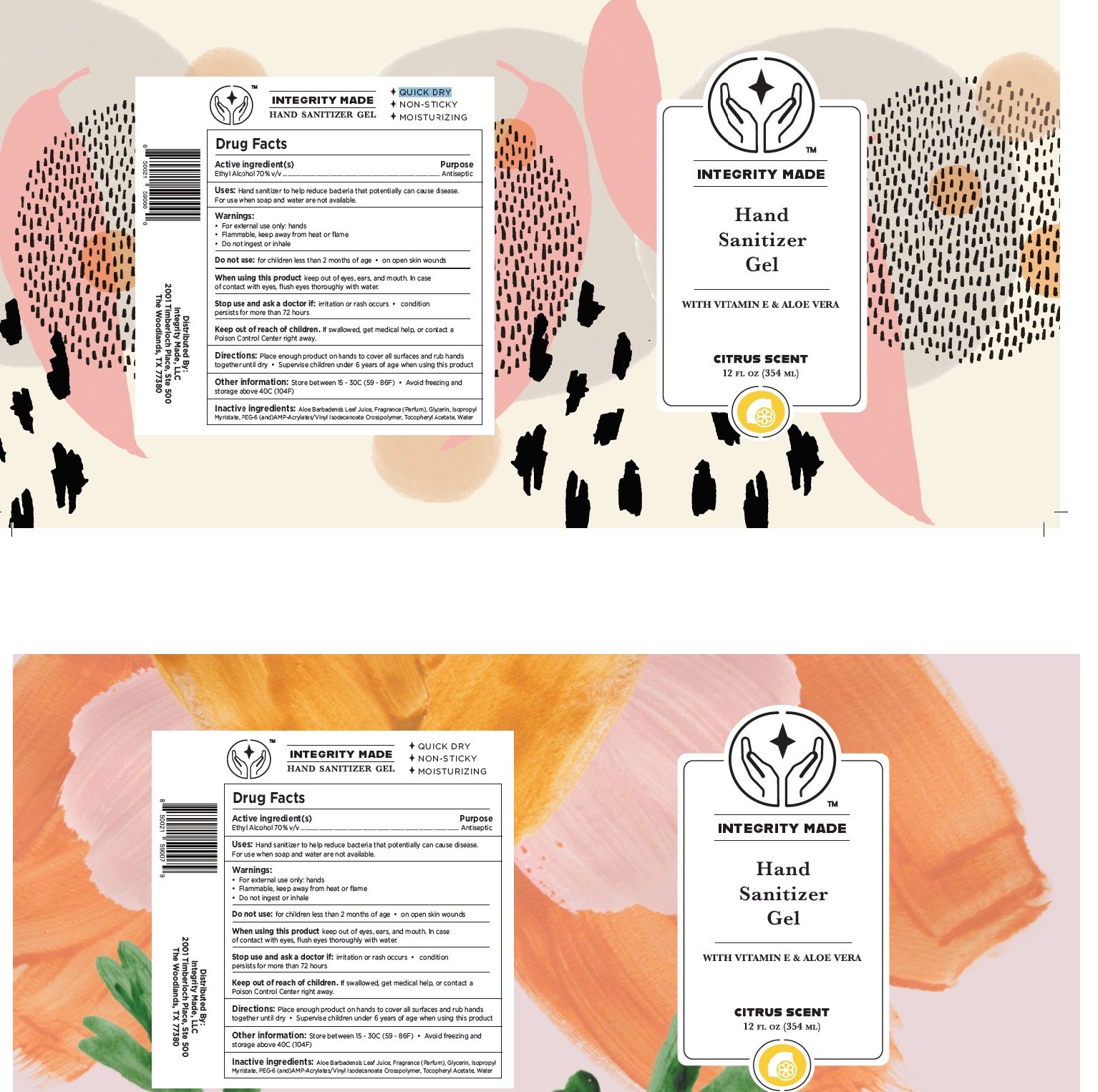 DRUG LABEL: Integrity Made LLC Citrus Scent with Aloe and  Vitamin E
NDC: 90118-003 | Form: GEL
Manufacturer: Integrity Made LLC
Category: otc | Type: HUMAN OTC DRUG LABEL
Date: 20200901

ACTIVE INGREDIENTS: ALCOHOL 0.7 mL/1 mL
INACTIVE INGREDIENTS: ALOE VERA LEAF; WATER; GLYCERIN; ISOPROPYL MYRISTATE; .ALPHA.-TOCOPHEROL ACETATE, DL-; RAPIDGEL EZ1

Integrity Made LLC Citrus Scent with Aloe and Vitamin E

Drug Active

Active Ingredients | Purpose
Ethyl Alcohol 70%v/v | Antiseptic

Uses:

- Hand sanitizer to help reduce bacteria that potentially can cause disease.
- For use when soap and water are not available.

Stop Use amd ask a doctor if

- irritation or rash occurs
- condition persists for more than 72 hours

Do not use

- For children less than 2 months of age
- on open skin wounds

Keep out of reach of children

If swallowed, get medical help, or contact a Posion ControlCenter Right Away

Uses:

Handsanitizer to help reduce bacteria that potentially can cause disease. For use when soap and wateer are not available

Warnings

- For external use only : hands
- Flammable keep away from heat or flame
- Do not ingest or inhale

Stop use and ask a doctor if

- irritation or rash occurs
- condition persists for more than 72 hours

STORAGE AND HANDLING

- Store between 15 - 30C (59 - 86 F)
- Avoidfreezing and storage above 40C (140F)

INACTIVE INGREDIENT

Aloe Barbadensis Leaf Juice

Fragrance

Glycerin

Isopropyl Myristate

PEG- and AMP- Acrylates/ Vinyl Isodecanoate crosspolymer

Tocopheryl Acetate

Water